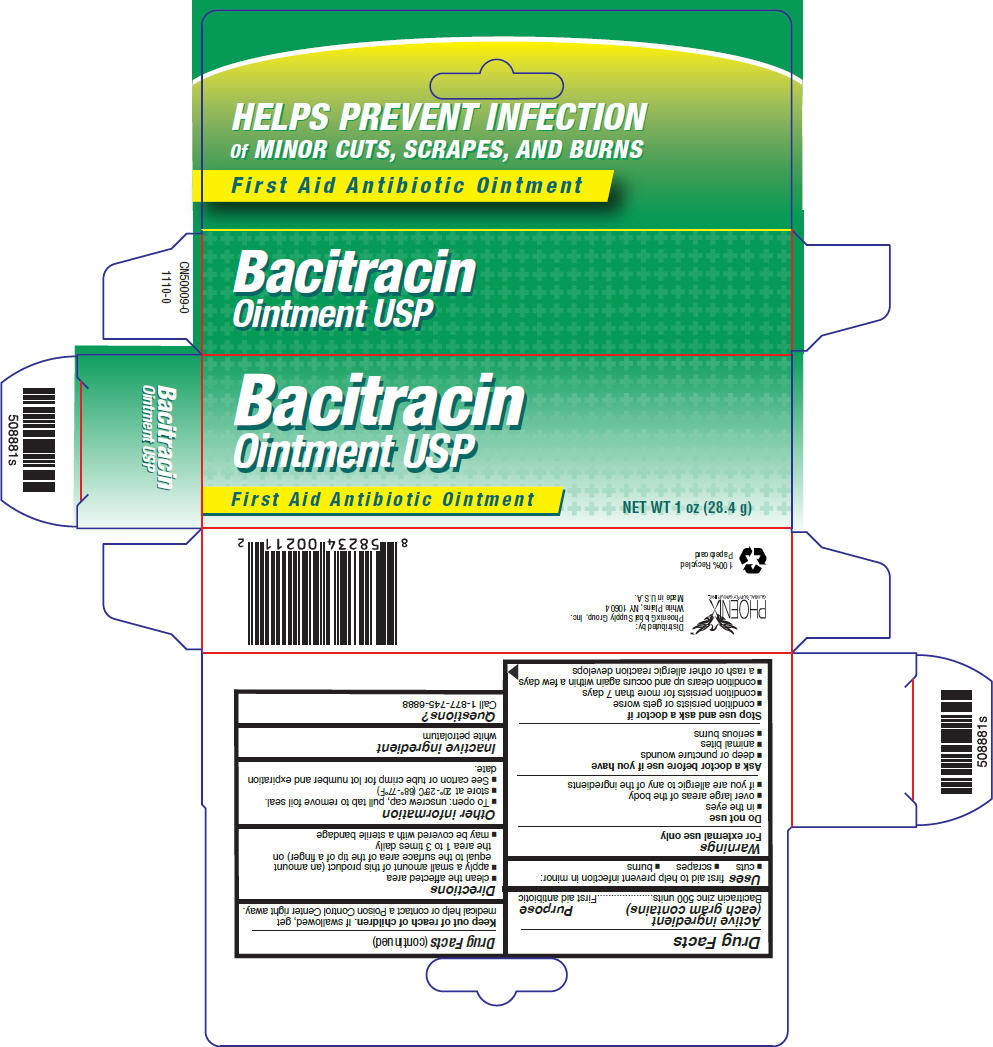 DRUG LABEL: Bacitracin
NDC: 52426-320 | Form: OINTMENT
Manufacturer: Phoenix Global Supply Group, Inc
Category: otc | Type: HUMAN OTC DRUG LABEL
Date: 20110421

ACTIVE INGREDIENTS: Bacitracin zinc 500 [iU]/1 g
INACTIVE INGREDIENTS: petrolatum

Bacitracin
Ointment USP

Drug Facts

Active ingredient (each gram contains)

Bacitracin zinc 500 units

Purpose

First aid antibiotic

Uses

first aid to help prevent infection in minor:

- cuts
- scrapes
- burns

Warnings

For external use only

Do not use

- in the eyes
- over large areas of the body
- if you are allergic to any of the ingredients

Ask a doctor before use if you have

- deep or puncture wounds
- animal bites
- serious burns

Stop use and ask a doctor if

- condition persists or gets worse
- condition persists for more than 7 days
- condition clears up and occurs again within a few days
- a rash or other allergic reaction develops

Keep out of reach of children. If swallowed, get medical help or contact a Poison Control Center right away.

Directions

- clean the affected area
- apply a small amount of this product (an amount equal to the surface area of the tip of a finger) on the area 1 to 3 times daily
- may be covered with a sterile bandage

Other information

- To open: unscrew cap, pull tab to remove foil seal.
- store at 20°-25°C (68°-77°F)
- See carton or tube crimp for lot number and expiration date.

Inactive ingredient

white petrolatum

Questions?

Call 1-877-745-6888

PRINCIPAL DISPLAY PANEL - 28.4 g Carton

Bacitracin
Ointment USP

First Aid Antibiotic Ointment

NET WT 1 oz (28.4 g)